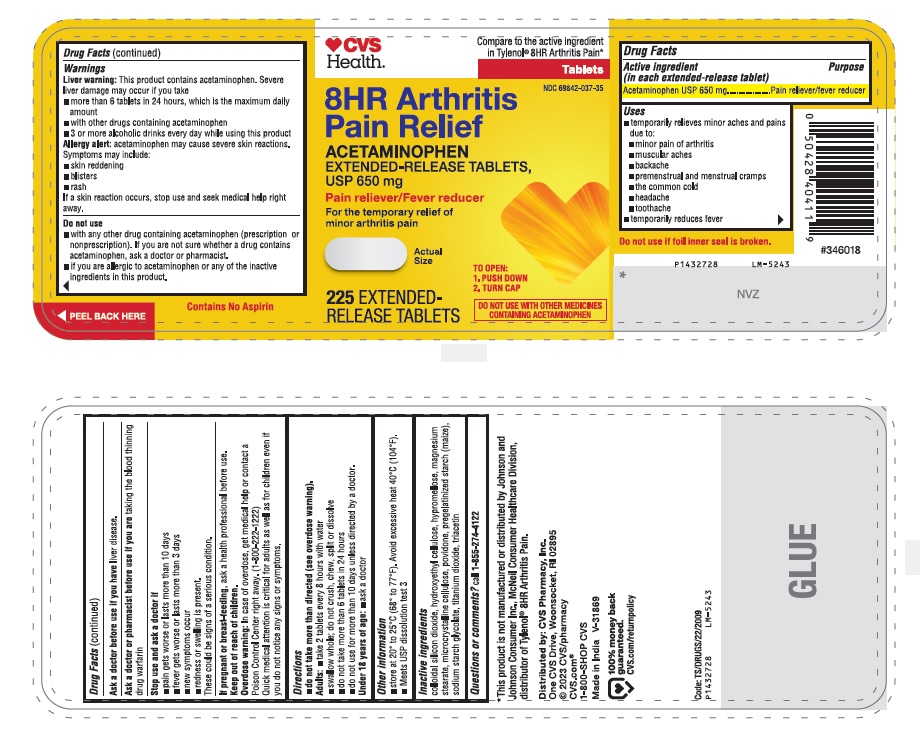 DRUG LABEL: Acetaminophen
NDC: 69842-037 | Form: TABLET, EXTENDED RELEASE
Manufacturer: CVS Pharmacy, Inc.
Category: otc | Type: Human OTC Drug Label
Date: 20240124

ACTIVE INGREDIENTS: ACETAMINOPHEN 650 mg/1 1
INACTIVE INGREDIENTS: SILICON DIOXIDE; HYDROXYETHYL CELLULOSE (140 MPA.S AT 5%); HYPROMELLOSE, UNSPECIFIED; MAGNESIUM STEARATE; MICROCRYSTALLINE CELLULOSE; POVIDONE, UNSPECIFIED; STARCH, CORN; SODIUM STARCH GLYCOLATE TYPE B POTATO; TITANIUM DIOXIDE; TRIACETIN

Drug Facts

Active ingredient (in each extended-release tablet)
Acetaminophen USP 650 mg

Purpose

Pain reliever/fever reducer

Uses

- temporarily relieves minor aches and pains due to:
  - minor pain of arthritis
  - muscular aches
  - backache
  - premenstrual and menstrual cramps
  - the common cold
  - headache
  - toothache
- temporarily reduces fever

Warnings

Liver warning: This product contains acetaminophen. Severe liver damage may occur if you take

- more than 6 tablets in 24 hours, which is the maximum daily amount
- with other drugs containing acetaminophen
- 3 or more alcoholic drinks every day while using this product

Allergy alert: acetaminophen may cause severe skin reactions. Symptoms may include:

- skin reddening
- blisters
- rash

If a skin reaction occurs, stop use and seek medical help right away.

Do not use

- with any other drug containing acetaminophen (prescription or nonprescription). If you are not sure whether a drug contains acetaminophen, ask a doctor or pharmacist.
- if you are allergic to acetaminophen or any of the inactive ingredients in this product.

Ask a doctor before use if you have liver disease.
Ask a doctor or pharmacist before use if you are taking the blood thinning drug warfarin

Stop use and ask a doctor if

- pain gets worse or lasts more than 10 days
- fever gets worse or lasts more than 3 days
- new symptoms occur
- redness or swelling is present

These could be signs of a serious condition.
If pregnant or breast-feeding, ask a health professional before use.

Keep out of reach of children.

Overdose warning: In case of overdose, get medical help or contact a Poison Control Center right away. (1-800-222-1222)
Quick medical attention is critical for adults as well as for children even if you do not notice any signs or symptoms.

Directions

- do not take more than directed (see overdose warning).

Adults:

- take 2 tablets every 8 hours with water
- swallow whole; do not crush, chew, split or dissolve
- do not take more than 6 tablets in 24 hours
- do not use for more than 10 days unless directed by a doctor.

Under 18 years of age:

- ask a doctor

Other information

- store at 20o to 25oC (68o to 77oF). Avoid excessive heat 40oC (104oF).
- do not use if carton is opened or foil inner seal is broken
- Meets USP dissolution test 3

Inactive ingredients

colloidal silicon dioxide, hydroxyethyl cellulose, hypromellose, magnesium stearate, microcrystalline cellulose, povidone, pregelatinized starch (maize), sodium starch glycolate, titanium dioxide, triacetin
Questions or comments?
call 1-855-274-4122
Distributed by: CVS Pharmacy, Inc.
One CVS Drive, Woonsocket, Rl 02895
©2023 CVS/pharmacy
CVS.com® 1-800-SHOP CVS
Made in India
Code: TS/DRUGS/22/2009

PACKAGE LABEL-PRINCIPAL DISPLAY PANEL - 650 mg (225 Tablet Bottle)

♥CVS
Health®
Compare to the active ingredient
in Tylenol® 8HR Arthritis Pain*
Tablets
NDC 69842-037-35
8HR Arthritis
Pain Relief
ACETAMINOPHEN
EXTENDED-RELEASE TABLETS,
USP 650 mg
Pain Reliever/Fever Reducer
For the temporary relief of
minor arthritis pain
Actual
Size
TO OPEN:
1. PUSH DOWN
2. TURN CAP

225 EXTENDED-
RELEASE TABLETS
DO NOT USE WITH OTHER MEDICINES
CONTAINING ACETAMINOPHEN